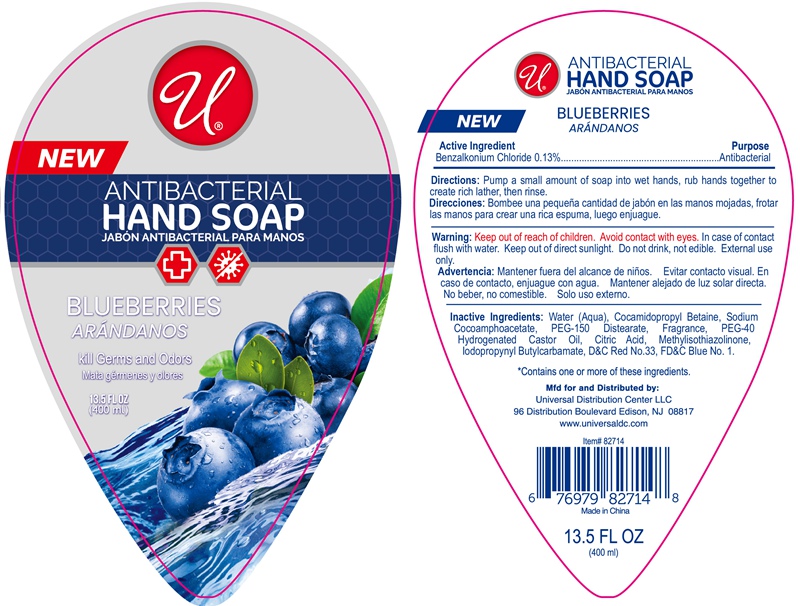 DRUG LABEL: ANTIBACTERIAL HAND BLUEBERRIES
NDC: 76176-046 | Form: LIQUID
Manufacturer: NINGBO LIYUAN DAILY CHEMICAL PRODUCTS CO., LTD.
Category: otc | Type: HUMAN OTC DRUG LABEL
Date: 20240101

ACTIVE INGREDIENTS: BENZALKONIUM CHLORIDE 0.13 g/100 mL
INACTIVE INGREDIENTS: WATER; COCAMIDOPROPYL BETAINE; SODIUM COCOAMPHOACETATE; IODOPROPYNYL BUTYLCARBAMATE; CITRIC ACID MONOHYDRATE; METHYLISOTHIAZOLINONE; D&C RED NO. 33; FD&C BLUE NO. 1; PEG-150 DISTEARATE; HYDROGENATED CASTOR OIL

Active Ingredient

Benzalkonium Chloride 0.13 percent

Purpose

Antibacterial

INDICATIONS AND USAGE

kill germs and odors

Directions:

Pump a small amount of soap into wet hands, rub hands together to create rich lather, then rinse.

Warning:

Aoid contact with eyes. In case of contact, flush with water.

Keep out of direct sunlight.

Do not drink, not edible.

External use only.

Inactive ingredients

Water (Aqua), Cocamidopropyl Betaine, Sodium Cocoamphoacetate, PEG-150 Distearate, Fragrance, PEG-40 Hydrogenated Castor Oil, Citric Acid, Methylisothiazolinone, Iodopropynyl Butylcarbamate, D&C Red No. 33, FD&C Blue No.1